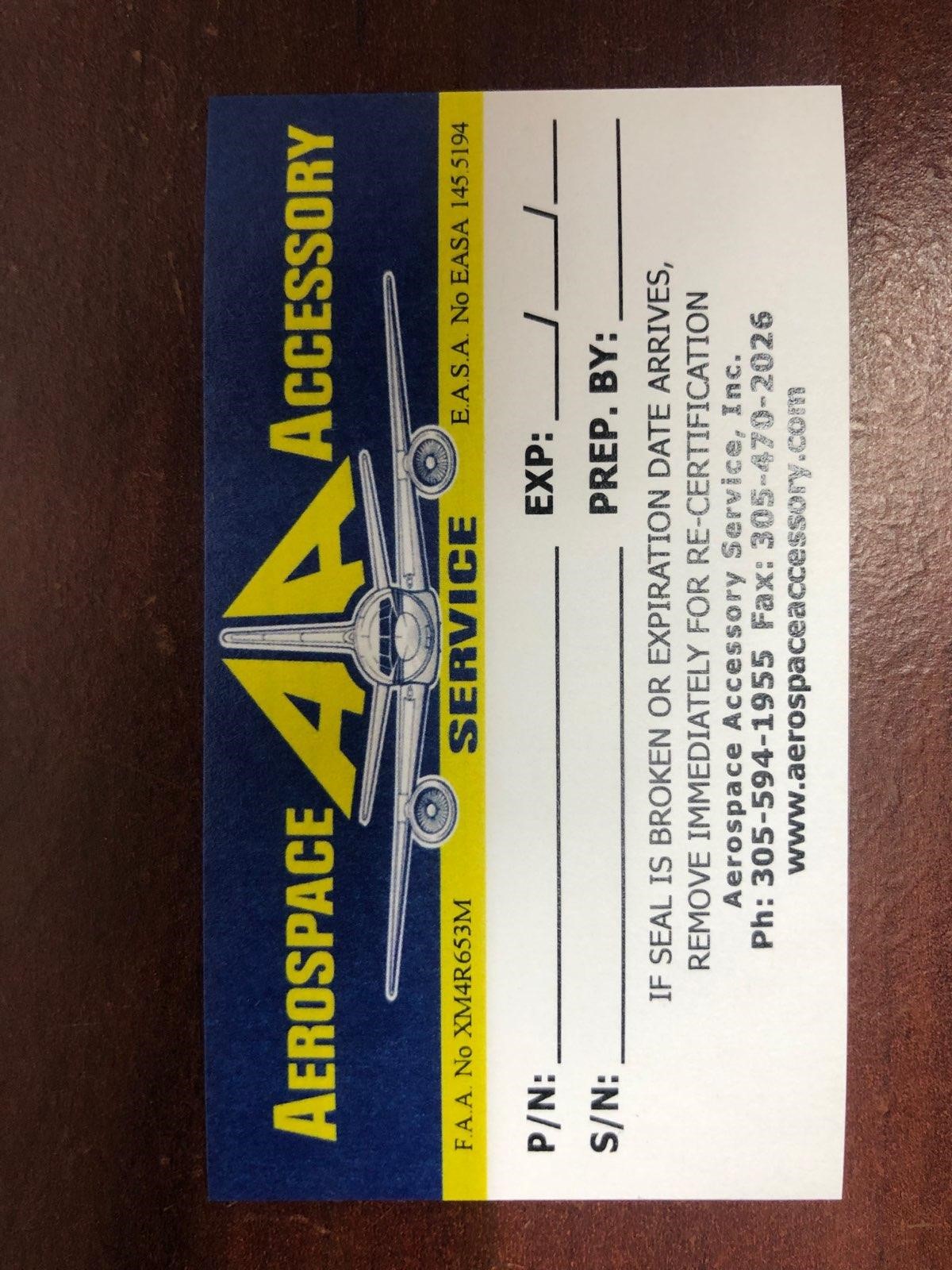 DRUG LABEL: Model 2004FAA Model 3-EEMK Model 3-EEMK-1 Model AA-8565 Model AA-8565-LATAM Model AWFAREMK Model CHAUTAUQUAEMK Model emk1000-10 Model FAREMK Model PMONTFAREMK Model SWEEMK Model SWEEMK-1 Model QXEMK Model G4FAREMK Model AA-8565 (excluding Miami Air)
NDC: 27860-001 | Form: KIT | Route: INTRAVENOUS
Manufacturer: Aerospace Accessory Service, Inc
Category: other | Type: MEDICAL DEVICE
Date: 20210518

ACTIVE INGREDIENTS: SODIUM CHLORIDE 9 g/1000 mL; SODIUM CHLORIDE 0.9 g/100 mL; ATROPINE SULFATE 0.1 mg/1 mL; Atropine Sulfate 0.1 mg/1 mL; Epinephrine 0.1 mg/1 mL; Epinephrine 0.1 mg/1 mL; EPINEPHRINE 0.1 mg/1 mL; LIDOCAINE HYDROCHLORIDE 20 mg/1 mL; LIDOCAINE HYDROCHLORIDE 20 mg/1 mL; LIDOCAINE HYDROCHLORIDE 20 mg/1 mL; DEXTROSE MONOHYDRATE 500 mg/1 mL; DEXTROSE MONOHYDRATE 25 g/50 mL; NITROGLYCERIN 0.4 mg/1 1; DIPHENHYDRAMINE HYDROCHLORIDE 50 mg/1 mL; Epinephrine 1 mg/1 mL; DIPHENHYDRAMINE HYDROCHLORIDE 25 mg/1 1; ISOPROPYL ALCOHOL 0.7 mL/1 mL; ACETAMINOPHEN 325 mg/1 1; ASPIRIN 325 mg/1 1; ASPIRIN 325 mg/1 1; ALBUTEROL SULFATE 90 ug/1 1; ALBUTEROL SULFATE 90 ug/1 1; ALBUTEROL SULFATE 90 ug/1 1; ALBUTEROL SULFATE 90 ug/1 1; ALBUTEROL SULFATE 108 ug/1 1; ALBUTEROL SULFATE 108 ug/1 1; ALBUTEROL SULFATE 90 ug/1 1
INACTIVE INGREDIENTS: WATER; WATER; SODIUM CHLORIDE; SODIUM HYDROXIDE; SULFURIC ACID; WATER; Sodium Bisulfite; Sodium Chloride; Hydrochloric Acid; Sodium Citrate; Citric Acid Monohydrate; Sodium Chloride; SODIUM METABISULFITE; ANHYDROUS CITRIC ACID; TRISODIUM CITRATE DIHYDRATE; SODIUM CHLORIDE; SODIUM METABISULFITE; ANHYDROUS CITRIC ACID; TRISODIUM CITRATE DIHYDRATE; SODIUM HYDROXIDE; HYDROCHLORIC ACID; SODIUM CHLORIDE; SODIUM CHLORIDE; HYDROCHLORIC ACID; SODIUM HYDROXIDE; HYDROCHLORIC ACID; SODIUM HYDROXIDE; Water; WATER; SODIUM HYDROXIDE; HYDROCHLORIC ACID; CALCIUM STEARATE; CROSCARMELLOSE SODIUM; LACTOSE MONOHYDRATE; SILICA DIMETHYL SILYLATE; BENZETHONIUM CHLORIDE; WATER; SODIUM HYDROXIDE; HYDROCHLORIC ACID; Sodium Chloride; Hydrochloric Acid; Water; CELLULOSE, MICROCRYSTALLINE; CROSCARMELLOSE SODIUM; D&C RED NO. 27; HYPROMELLOSES; LACTOSE; MAGNESIUM STEARATE; POLYETHYLENE GLYCOL, UNSPECIFIED; SILICON DIOXIDE; TITANIUM DIOXIDE; WATER; HYPROMELLOSES; POLYETHYLENE GLYCOL, UNSPECIFIED; POVIDONE, UNSPECIFIED; SODIUM STARCH GLYCOLATE TYPE A POTATO; STARCH, CORN; STEARIC ACID; TITANIUM DIOXIDE; CELLULOSE, MICROCRYSTALLINE; CROSCARMELLOSE SODIUM; HYPROMELLOSES; MINERAL OIL; STARCH, CORN; TITANIUM DIOXIDE; STARCH, CORN; POLYETHYLENE GLYCOL, UNSPECIFIED; PROPYLENE GLYCOL; HYPROMELLOSE, UNSPECIFIED; NORFLURANE; NORFLURANE; ALCOHOL; NORFLURANE; NORFLURANE; ALCOHOL; OLEIC ACID; NORFLURANE; ALCOHOL; OLEIC ACID; NORFLURANE; ALCOHOL; NORFLURANE; ALCOHOL

Model 2004FAA
Model 3-EEMK
Model 3-EEMK-1
Model AA-8565
Model AA-8565-LATAM
Model AWFAREMK
Model CHAUTAUQUAEMK
Model emk1000-10
Model FAREMK
Model PMONTFAREMK
Model SWEEMK
Model SWEEMK-1
Model QXEMK
Model G4FAREMK
Model AA-8565 (excluding Miami Air)

Aerospace Accessory Service

P/N:

S/N:

EXP:

Prep. By: